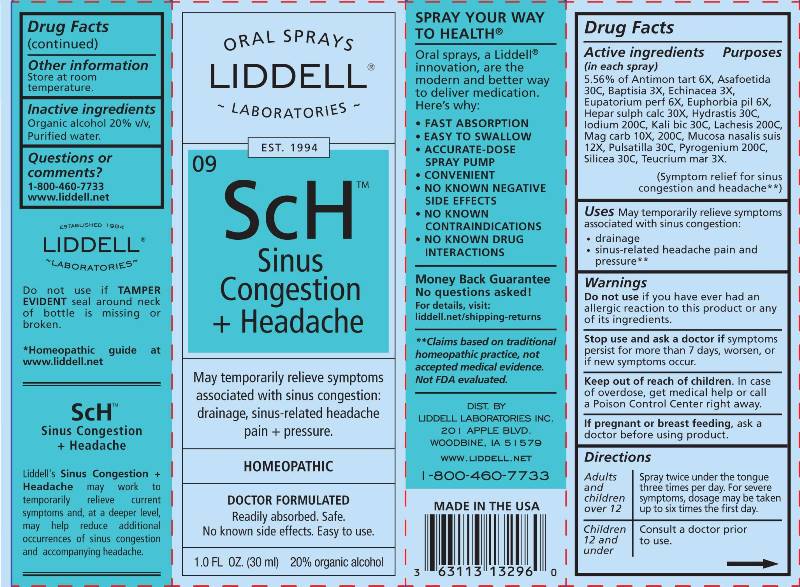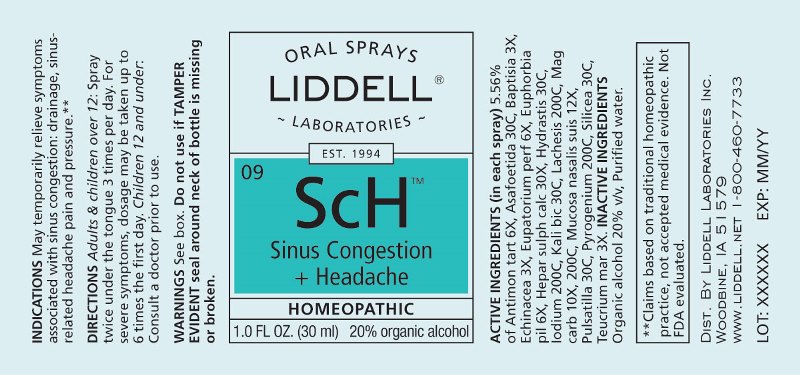 DRUG LABEL: Sinus Congestion Headache
NDC: 50845-0263 | Form: SPRAY
Manufacturer: Liddell Laboratories, Inc.
Category: homeopathic | Type: HUMAN OTC DRUG LABEL
Date: 20241104

ACTIVE INGREDIENTS: ANTIMONY POTASSIUM TARTRATE 6 [hp_X]/1 mL; FERULA ASSA-FOETIDA RESIN 30 [hp_C]/1 mL; BAPTISIA TINCTORIA ROOT 3 [hp_X]/1 mL; ECHINACEA ANGUSTIFOLIA WHOLE 3 [hp_X]/1 mL; EUPATORIUM PERFOLIATUM FLOWERING TOP 6 [hp_X]/1 mL; EUPHORBIA HIRTA FLOWERING TOP 6 [hp_X]/1 mL; CALCIUM SULFIDE 30 [hp_X]/1 mL; GOLDENSEAL 30 [hp_C]/1 mL; IODINE 200 [hp_C]/1 mL; POTASSIUM DICHROMATE 30 [hp_X]/1 mL; LACHESIS MUTA VENOM 200 [hp_C]/1 mL; MAGNESIUM CARBONATE 10 [hp_X]/1 mL; SUS SCROFA NASAL MUCOSA 12 [hp_X]/1 mL; PULSATILLA PRATENSIS WHOLE 30 [hp_C]/1 mL; RANCID BEEF 200 [hp_C]/1 mL; SILICON DIOXIDE 30 [hp_C]/1 mL; TEUCRIUM MARUM WHOLE 3 [hp_X]/1 mL
INACTIVE INGREDIENTS: WATER; ALCOHOL

DRUG FACTS:

ACTIVE INGREDIENTS:

(in each spray) 5.56% of Antimonium Tartaricum 6X, Asafoetida 30C, Baptisia Tinctoria 3X, Echinacea (Angustifolia) 3X, Eupatorium Perfoliatum 6X, Euphorbia Pilulifera 6X, Hepar Sulphuris Calcareum 30X, Hydrastis Canadensis 30C, Iodium 200C, Kali Bichromicum 30C, Lachesis Mutus 200C, Magnesia Carbonica 10X, 200C, Mucosa Nasalis Suis 12X, Pulsatilla (Pratensis) 30C, Pyrogenium 200C, Silicea 30C, Teucrium Marum 3X.

USES:

May temporarily relieve these symptoms associated with sinus congestion: drainage, sinus related headache pain and pressure.**

**Claims based on traditional homeopathic practice, not accepted medical evidence. Not FDA evaluated.

WARNINGS:

Do not use if you have ever had an allergic reaction to this product or any of its ingredients.

Stop use and ask a doctor if symptoms persist for more than 7 days, worsen or if new symptoms occur.

Keep out of reach of children. In case of overdose, get medical help or call a Poison Control Center right away.

If pregnant or breast feeding, ask a doctor before using this product.

Do not use if TAMPER EVIDENT seal around neck of bottle is missing or broken.

Store at room temperature.

Keep out of reach of children. In case of overdose, get medical help or call a Poison Control Center right away.

DIRECTIONS:

Adults and children over 12: Spray twice under the tongue 3 times per day. For severe symptoms, dosage may be taken up to 6 times the first day.

Children 12 and under: Consult a doctor prior to use.

INDICATIONS:

May temporarily relieve these symptoms associated with sinus congestion: drainage, sinus related headache pain and pressure.**

**Claims based on traditional homeopathic practice, not accepted medical evidence. Not FDA evaluated.

INACTIVE INGREDIENTS:

Organic alcohol 20% v/v, Purified water.

QUESTIONS:

DIST. BY

LIDDELL LABORATORIES, INC.

201 APPLE BLVD.

WOODBINE, IA 51579

WWW.LIDDELL.NET

1-800-460-7733

PACKAGE LABEL DISPLAY:

ORAL SPRAYS
LIDDELL
LABORATORIES

EST. 1994

09 ScH
Sinus
Congestion
+ Headache

HOMEOPATHIC

DOCTOR FORMULATED

Readily absorbed. Safe.
No known side effects. Easy to use.

1.0 FL OZ. (30 ml)